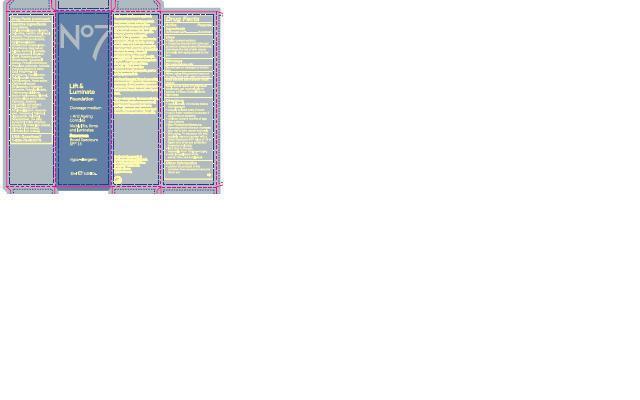 DRUG LABEL: No7 Lift and Luminate Foundation Sunscreen Broad Spectrum SPF 15 Toffee
NDC: 61589-6016 | Form: CREAM
Manufacturer: BCM Cosmetique SAS
Category: otc | Type: HUMAN OTC DRUG LABEL
Date: 20131210

ACTIVE INGREDIENTS: Octinoxate 7.5 g/30 g
INACTIVE INGREDIENTS: WATER; CYCLOMETHICONE 5; GLYCERIN; TALC; MICA; LECITHIN, SOYBEAN; ETHYLHEXYL STEARATE; TRIHYDROXYSTEARIN; DISTEARDIMONIUM HECTORITE; CYCLOMETHICONE 6; DIMETHICONE/DIENE DIMETHICONE CROSSPOLYMER; DIMETHICONE; MAGNESIUM SULFATE; ASCORBYL GLUCOSIDE; PHENOXYETHANOL; BUTYLENE GLYCOL; PEG/PPG-18/18 DIMETHICONE; .ALPHA.-TOCOPHEROL ACETATE; PHENYL TRIMETHICONE; PROPYLENE CARBONATE; ACTINIDIA CHINENSIS WHOLE; CETYL PEG/PPG-10/1 DIMETHICONE (HLB 2); HEXYL LAURATE; POLYGLYCERYL-4 ISOSTEARATE; METHYLPARABEN; AVENA SATIVA WHOLE; ETHYLPARABEN; POTASSIUM HYDROXIDE; VITAMIN A PALMITATE; TRIETHOXYCAPRYLYLSILANE; HYALURONATE SODIUM; ALCOHOL; LUPINUS ALBUS SEED; CARBOMER 934; POLYSORBATE 20; ETHYLHEXYLGLYCERIN; ASCORBIC ACID; TOCOPHEROL; PALMITOYL OLIGOPEPTIDE; PALMITOYL TETRAPEPTIDE-7; FERRIC OXIDE YELLOW; TITANIUM DIOXIDE; FERRIC OXIDE RED; FERROSOFERRIC OXIDE

No7 Lift and Luminate Foundation Sunscreen Broad Spectrum SPF15 Toffee

Carton Active Ingredients Section

Active Ingredients

Octinoxate 7.5%

Uses

Uses - helps prevent sunburn

Warnings

For external use only

Do not use on damaged or broken skin

When using this product keep out of eyes. Rinse with water to remove

Ask a doctor

Stop use and ask a doctor if rash occurs.

Keep out of reach of children. If swallowed, get medical help or contact a Poison Control Center right away.

Directions

Directions for suncreen use

apply liberally 15 minutes before sun exposure

reapply at least every 2 hours

use a water resistant sunscreen if swimming or sweating

children under 6 monhts of age: Ask a doctor

Sun Protection Measures. Spending time in the sun increases your risk of skin cancer and early skin aging. To decrease this risk, regularly use a sunscreen with a Broad Spectrum SPF value of 15 or higher and other sun protection measures including:

limit time in the sun, especially from 10 a.m. - 2 p.m.

wear long-sleeved shirts, pants, hats, and sunglasses

Other information

Protect the product in this container from excessive heat and direct sun

Inactive ingredients

Aqua(Water), Cyclopentasiloxane, Glycerin, Talc, Mica, Lecithin, Ethylhexyl stearate, Trihydroxystearin, Disteardimonium hectorite, Cyclohexasiloxane, Dimethicone crosspolymer, Dimethicone, Magnesium sulfate, Ascorbyl glucoside, Phenoxyethanol, Butylene glycol, PEG/PPG-18/18 Dimethicone, Tocopheryl acetate, Phenyl trimethicone, Propylene carbonate, Actinidia chinensis(Kiwi) fruit water, Cetyl PEG/PPG-10/1 dimethicone, Hexyl laurate, Polyglyceryl-4 isostearate, Methylparaben, Avena sativa (Oat) kernel extract, Ethylparaben, Potassium hydroxide, Retinyl palmitate, Triethoxycaprylylsilane, Sodium hyaluronate, Alcohol, Lupinus albus seed extract, Carbomer, Sophora angustifolia root extract, Polysorbate 20, BT, Ethylhexylglycerin, Ascorbic acid, Tocopherol, Palmitoyl oligopeptide, Palmitoyl tetrapeptide-7, CI 77492(Iron oxides), CI 77891(Titanium dioxide) CI 77491(Iron oxides)CI 77499(Iron oxides)

Description

A luminating foundation which has been formulated with a polymer to help appear to visibly lift and give firmer feeling skin. Our Pro-retinol complex containing Lipopeptides boosts and maintains elasticity. It also contains a brightening complex to give skin a long term boost for even skin tone. Powerful antioxidants, Vitamin C and E, and SPF 15 help protect against the ageing effects of free radicals. Minimises the appearance of age spots, pores and pigmentation.

For Best Results: Blend smoothly and evenly with your fingers or a sponge, working downwards and outwards from the centre of your face.

Hypoallergenic: Because all skin can have sensitive moments all our foundation products are hypo-allergenic so they are kind to even the most sensitive skin.

Information

The Boots Company PLC

Nottingham England NG2 3AA

Dist. by Boots Retail USa Inc.

Norwalk CT 06851 USA

Made in France

www.boots.com

Jar label

No7 Lift & Luminate Foundation Sunscreen Broad Spectrum SPF 15

30ml e 1 US Fl.Oz.

Active ingredients: Octinoxate 7.5%

Warnings

warning: Avoid contact with eyes. If product gets into the eyes, rinse well with water immediately.

Description

Firmer, even skin with a youthful glow, visibly firms, lifts and brightens for a more luminous complexion

Information

The Boots Company PLC

Nottingham England NG2 3AA.

Dist. by Boots Retail USA Inc.

Norwalk CT 06851 USA

Made in france

www.boots.com